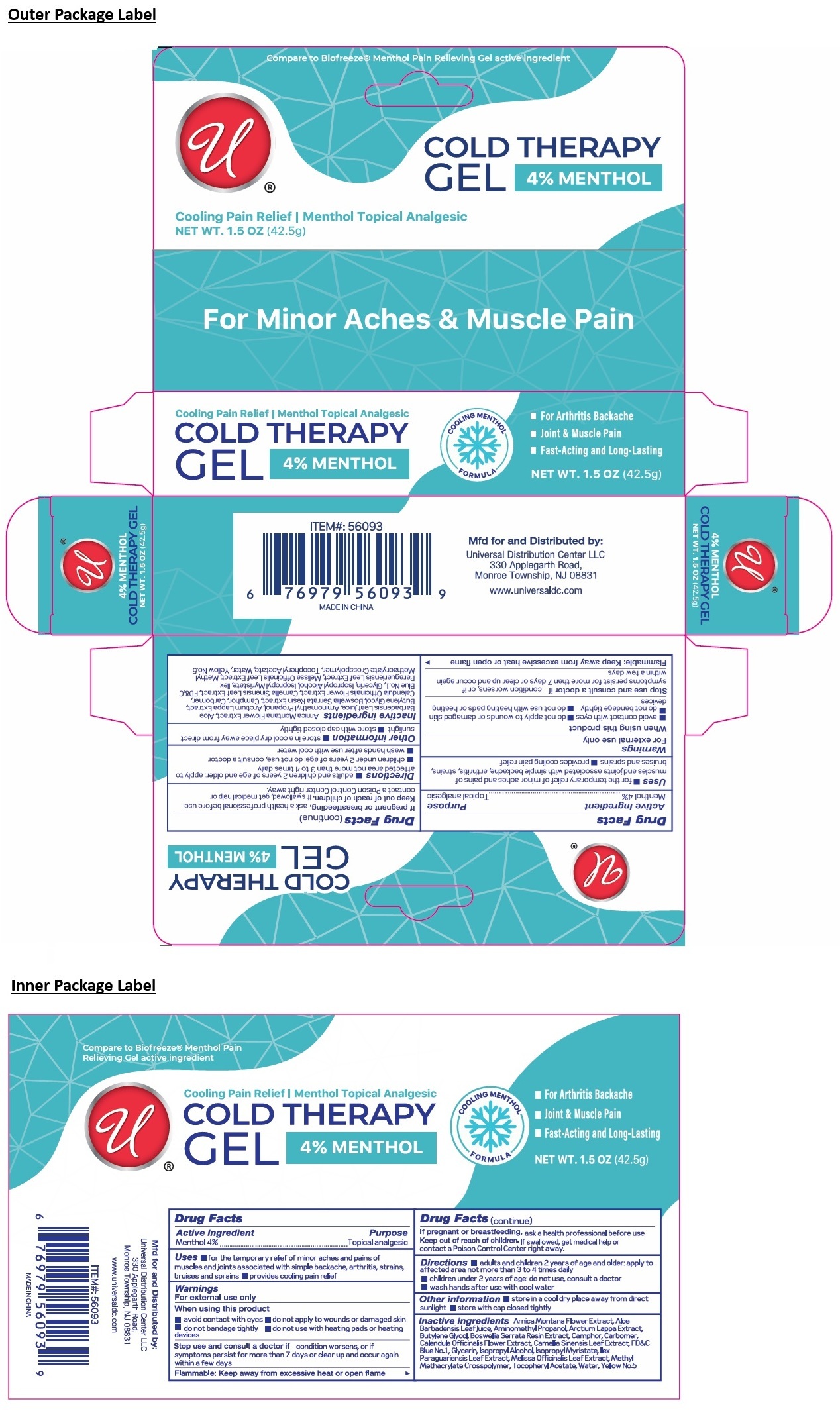 DRUG LABEL: 4% MENTHOL COLD THERAPY
NDC: 43473-098 | Form: GEL
Manufacturer: Nantong Health & Beyond Hygienic Products Inc.
Category: otc | Type: HUMAN OTC DRUG LABEL
Date: 20260205

ACTIVE INGREDIENTS: MENTHOL, UNSPECIFIED FORM 4 g/100 g
INACTIVE INGREDIENTS: ARNICA MONTANA FLOWER; ALOE VERA LEAF JUICE; AMINOMETHYLPROPANOL; ARCTIUM LAPPA WHOLE; BUTYLENE GLYCOL; INDIAN FRANKINCENSE; CAMPHOR (NATURAL); CARBOMER HOMOPOLYMER, UNSPECIFIED TYPE; CALENDULA OFFICINALIS FLOWER; GREEN TEA LEAF; FD&C BLUE NO. 1; GLYCERIN; ISOPROPYL ALCOHOL; ISOPROPYL MYRISTATE; ILEX PARAGUARIENSIS LEAF; MELISSA OFFICINALIS LEAF; METHYL METHACRYLATE/GLYCOL DIMETHACRYLATE CROSSPOLYMER; .ALPHA.-TOCOPHEROL ACETATE; WATER; FD&C YELLOW NO. 5

43473-098 4% MENTHOL COLD THERAPY GEL

Active Ingredient

Menthol 4%

Purpose

Topical analgesic

Uses

• for the temporary relief of minor aches and pains of muscles and joints associated with simple backache, arthritis, strains, bruises and sprains • provides cooling pain relief

Warnings

For external use only

When using this product
• avoid contact with eyes • do not apply to wounds or damaged skin
• do not bandage tightly • do not use with heating pads or heating devices

Stop use and consult a doctor ifcondition worsens, or if symptoms persist for more than 7 days or clear up and occur again within a few days

Flammable: Keep away from excessive heat or open flame

If pregnant or breastfeeding,ask a health professional before use.

Keep out of reach of children.If swallowed, get medical help or contact a Poison Control Center right away.

Directions

• adults and children 2 years of age and older: apply to affected area not more than 3 to 4 times daily
• children under 2 years of age: do not use, consult a doctor
• wash hands after use with cool water

Other information

• store in a cool dry place away from direct sunlight • store with cap closed tightly

Inactive ingredients

Arnica Montana Flower Extract, Aloe Barbadensis Leaf Juice, Aminomethyl Propanol, Arctium Lappa Extract, Butylene Glycol, Boswellia Serrata Resin Extract, Camphor, Carbomer, Calendula Officinalis Flower Extract, Camellia Sinensis Leaf Extract, FD&C Blue No.1, Glycerin, Isopropyl Alcohol, Isopropyl Myristate, Ilex Paraguariensis Leaf Extract, Melissa Officinalis Leaf Extract, Methyl Methacrylate Crosspolymer, Tocopheryl Acetate, Water, Yellow No.5

Compare to Biofreeze® Menthol Pain Relieving Gel active ingredient

Cooling Pain Relief | Menthol Topical Analgesic

For Minor Aches & Muscle Pain

COOLING MENTHOL FORMULA

• For Arthritis Backache
• Joint & Muscle Pain
• Fast-Acting and Long-Lasting

Mfd for and Distributed by:
Universal Distribution Center LLC
330 Applegarth Road,
Monroe Township, NJ 08831

www.universaldc.com

MADE IN CHINA